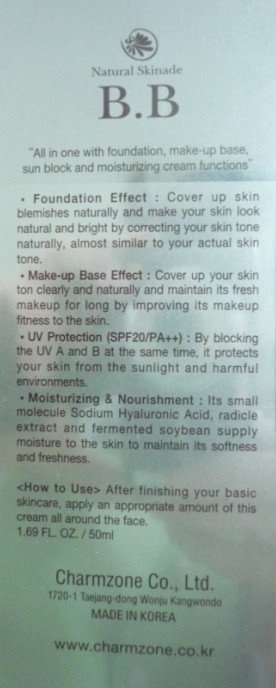 DRUG LABEL: Charmzone Natural Skinade BB Cream (SPF20 PA)
NDC: 22201-1001 | Form: CREAM
Manufacturer: CHARMZONE CO LTD
Category: otc | Type: HUMAN OTC DRUG LABEL
Date: 20091109

ACTIVE INGREDIENTS: TITANIUM DIOXIDE 3.11 mL/50 mL; ZINC OXIDE 0.777 mL/50 mL

ACTIVE INGREDIENT

INGREDIENTS:

WATER, CYCLOMETHICONE, GLYCERIN, DIMETHICONE, TITANIUM DIOXIDE, CYCLOPENTASILOXANE, TALC, BUTYLENE GLYCOL, CETYL PEG/PPG-10/1 DIMETHICONE, ZINC OXIDE, BEESWAX, HYDROGENATED POLYDECENE, POLYSILICONE-11, IRON OXIDES, PEG-7 DIMETHICONE, ULMUS DAVIDIANA ROOT EXTRACT, BACILLUS / SOYBEAN FERMENT EXTRACT, DIOSPYROS KAKI LEAF EXTRACT, TOCOPHERYL ACETATE, SORBITAN SESQUIOLEATE, ALUMINUM HYDROXIDE, BIFIDA FERMENT LYSATE, PHENOXYETHANOL, SODIUM CITRATE, SODIUM HYALURONATE, STEARIC ACID, METHYLPARABEN, ORYZANOL, PROPYLPARABEN, FOMES OFFICINALIS (MUSHROOM) EXTRACT, MYRISTIC ACID, DISODIUM EDTA, FRAGRANCE, STEARYL GLYCYRRHETINATE, DIPOTASSIUM GLYCYRRHIZATE, SODIUM HYDROLYZED HYALURONATE, CYCLOMETHICONE, METHYL PYRROLIDONE, BRASSICA CAMPESTRIS (RAPESEED) STEROLS, PEG-5 RAPESEED STEROL, ALCOHOL, PHYTOSPHINGOSINE ASCORBATE, CETETH-3, CETETH-5, HYDROGENATED LECITHIN, CHOLESTEROL, DEA-CETYL PHOSPHATE, BHT

WHEN USING

[How to Use]

After finishing your basic skincare, apply an appropriate amount of this cream all around the face.

KEEP OUT OF REACH OF CHILDREN

[CAUTION]

For external use only. Avoid contact with eyes. Keep out of children's reach.

PURPOSE

Benefits of Natural Skinade B.B Cream:

1. Foundation Effect: Cover up skin blemishes naturally and make your skin look natural and bright by correcting your skin tone naturally, almost similar to your actual skin tone.

2. Make-up Base Effect: Cover up your skin tone clearly and naturally and maintain its fresh makeup for long by improving its makeup fitness to the skin.

3. UV Protection (SPF20/PA++): By blocking the UV A and B at the same time, it protects your skin from the sunlight and harmful environments.

4. Moisturizing and Nourishment: Its small molecule Sodium Hyaluronic Acid, radicle extract and fermented soybean supply moisture to the skin to maintain its softness and freshness.

5. Skin Soothing and Sebum Control: By containing mushroom and persimmon leaf extract, it eliminates extra sebum and alleviates the skin to keep your skin fresh all day long.

PACKAGE LABEL

Label8